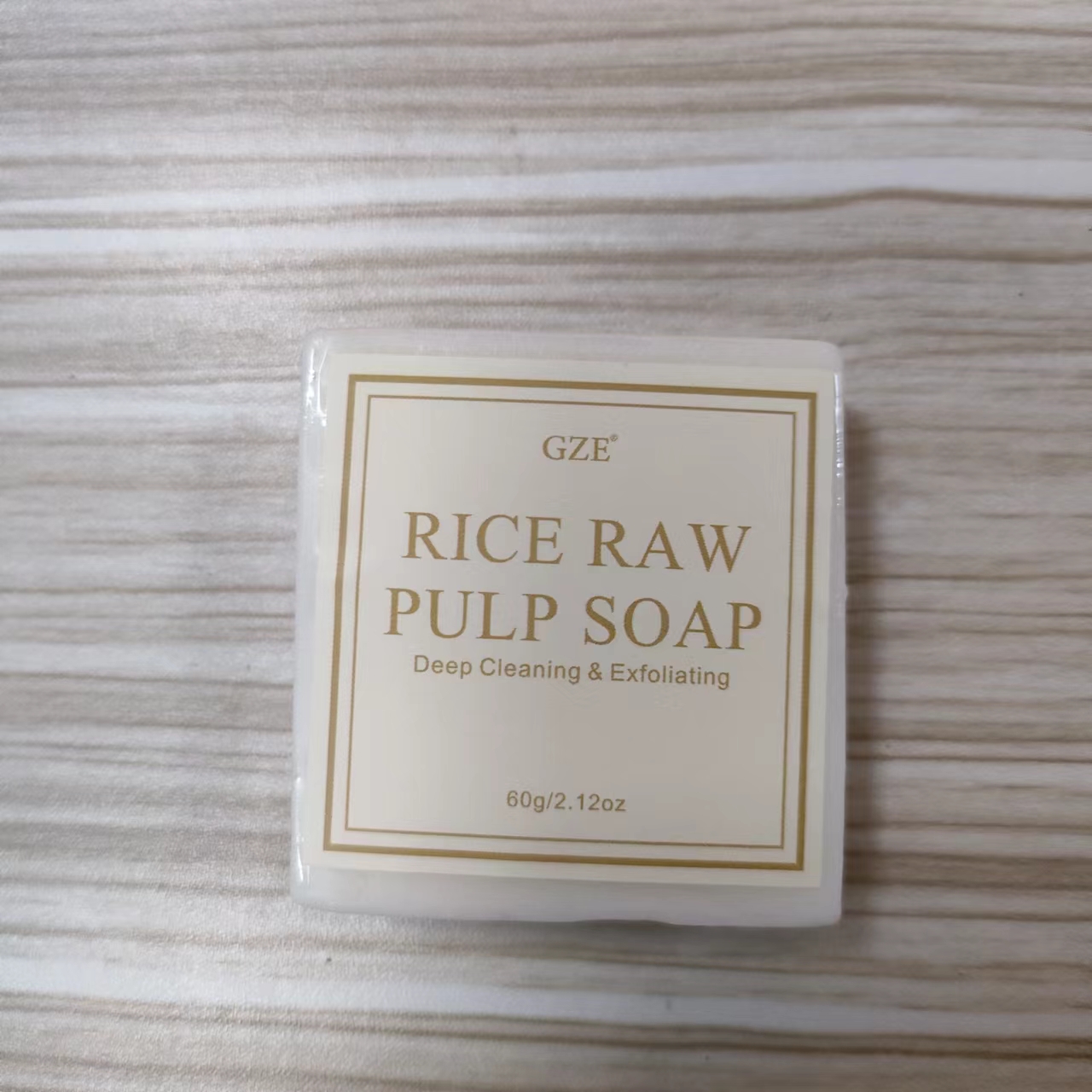 DRUG LABEL: GZE Rice Raw PulpSoap
NDC: 74458-096 | Form: SOAP
Manufacturer: Guangzhou Yilong Cosmetics Co., Ltd
Category: otc | Type: HUMAN OTC DRUG LABEL
Date: 20241113

ACTIVE INGREDIENTS: ORYZA SATIVA (RICE) HULL EXTRACT 8 g/100 g
INACTIVE INGREDIENTS: SORBITOL; SUCROSE; VITIS VINIFERA (GRAPE) SEED OIL; GLYCERIN; STEARIC ACID; OLEA EUROPAEA (OLIVE) FRUIT OIL; LAURIC ACID; AQUA; PROPYLENE GLYCOL; PRUNUS AMYGDALUS DULCIS (SWEET ALMOND) OIL

GZE RICE RAW PULP SOAP

ACTIVE INGREDIENT

Oryza Sativa (Rice) Extract

Sucrose

INDICATIONS AND USAGE

Wet your face and rice soap, rub the rice soap in your hands until it lathers, place the lather on your face and massage in a circular motion for 2-3 minutes. Finally, rinse off with water, dry and follow up with skincare.

INACTIVE INGREDIENT

Sorbitol

Propylene Glycol

Glycerol

Stearic Acid

Lauric Acid

Aqua

Olea Europaea (Olive) Fruit Oil

Prunus Amygdalus Dulcis (Sweet Almond) Oil

Vitis Vinifera (Grape) Seed Oil

Fragrance

PURPOSE

Exfoliating.

WARNINGS

For external use only.

Stop use and ask a doctor if rash occurs.

Do not use on damaged or broken skin.

When using this product keep out of eyes. Rinse with water to remove.

Keep out of reach of children. If swallowed, get medical help or contact a Poison Control Center right away.

DOSAGE AND ADMINISTRATION

Wet your face and rice soap, rub the rice soap in your hands until it lathers, place the lather on your face and massage in a circular motion for 2-3 minutes. Finally, rinse off with water, dry and follow up with skincare. Once every two weeks.